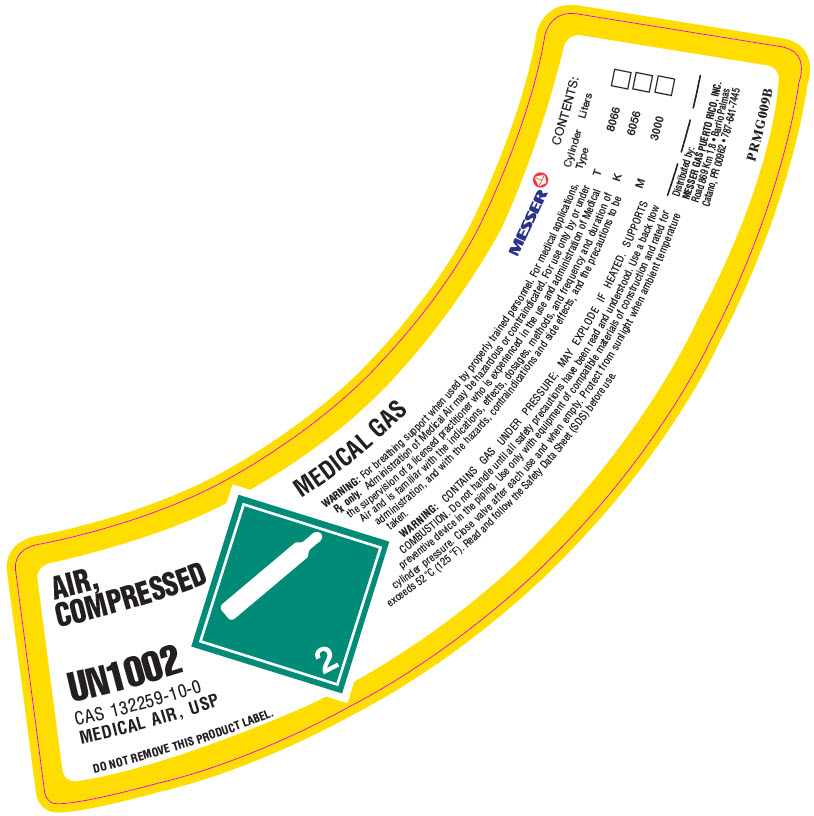 DRUG LABEL: Air, Compressed
NDC: 52374-906 | Form: GAS
Manufacturer: Messer Gas Puerto Rico Inc
Category: animal | Type: PRESCRIPTION ANIMAL DRUG LABEL
Date: 20211002

ACTIVE INGREDIENTS: Oxygen 21 L/100 L
INACTIVE INGREDIENTS: Nitrogen 79 L/100 L

AIR, COMPRESSED

WARNINGS AND PRECAUTIONS SECTION

WARNING: For breathing support when used by properly trained personnel. For medical applications, Rx only. Administration of Medical Air may be hazardous or contraindicated. For use only by or under the supervision of a licensed practitioner who is experienced in the use and administration of Medical Air and is familiar with the indications, effects, dosages, methods, and frequency and duration of administration, and with the hazards, contraindications and side effects, and the precautions to be taken.
WARNING: CONTAINS GAS UNDER PRESSURE; MAY EXPLODE IF HEATED. SUPPORTS COMBUSTION. Do not handle until all safety precautions have been read and understood. Use a back flow preventive device in the piping. Use only with equipment of compatible materials of construction and rated for cylinder pressure. Close valve after each use and when empty. Protect from sunlight when ambient temperature exceeds 52°C (125°F). Read and follow the Safety Data Sheet (SDS) before use.

Un-Coded Section

CONTENTS:
Cylinder Type | Liters
T | 8066 | [_]
K | 6056 | [_]
M | 3000 | [_]
______ | ______ | ______

Distributed by:
Messer Gas Puerto Rico Inc,
Road 869 Km 1.8,
Barrio Palmas, Catano PR 00962
(787-641-7445)
PRMG009B

PACKAGE LABEL.PRINCIPAL DISPLAY PANEL

Messer
AIR, COMPRESSED USP
UN1002
CAS 7727-37-9
MEDICAL AIR
DO NOT REMOVE THIS PRODUCT LABEL.
MEDICAL GAS